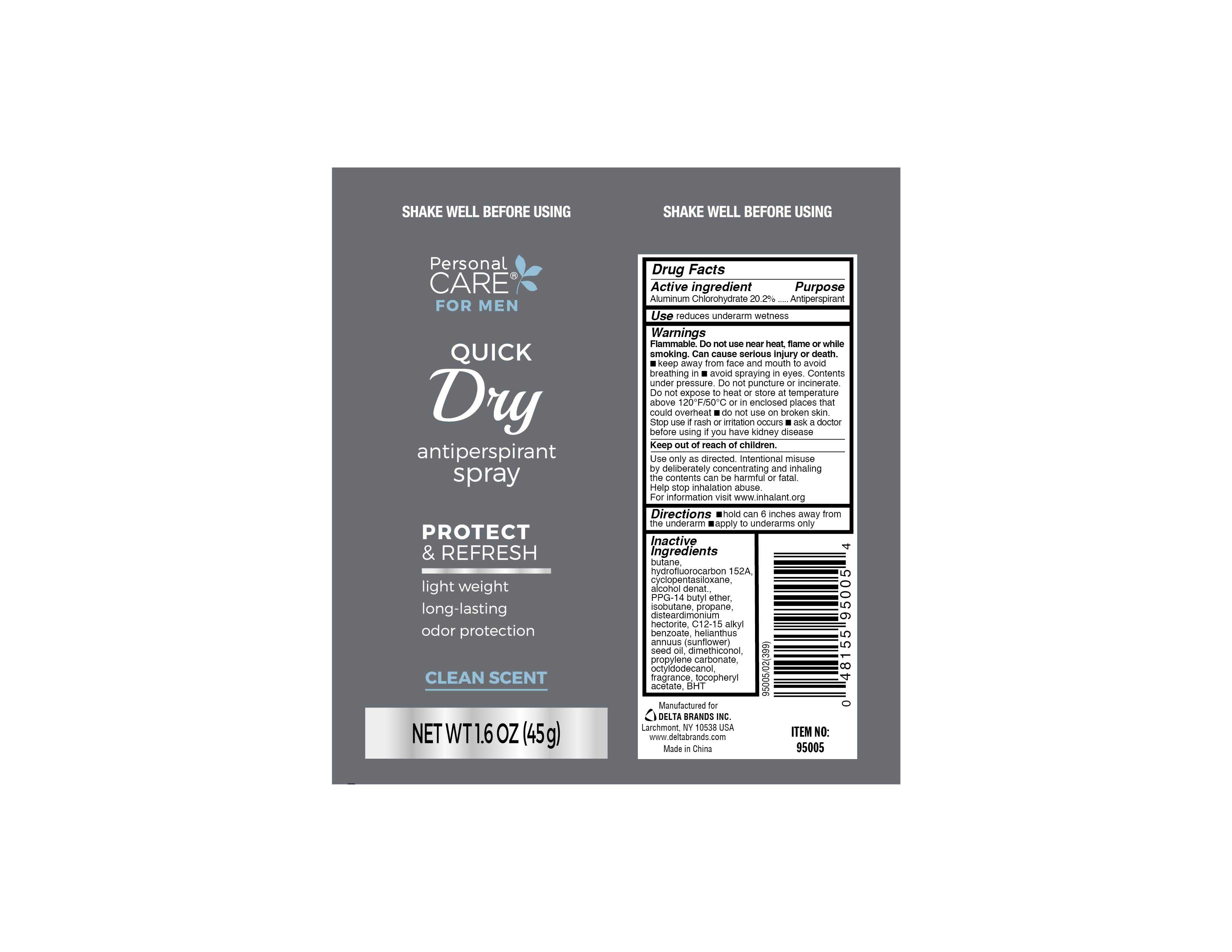 DRUG LABEL: Personal CARE
NDC: 20276-906 | Form: SPRAY
Manufacturer: Delta Brands Inc
Category: otc | Type: HUMAN OTC DRUG LABEL
Date: 20190206

ACTIVE INGREDIENTS: ALUMINUM CHLOROHYDRATE 20.2 g/100 g
INACTIVE INGREDIENTS: BUTANE; 1,1-DIFLUOROETHANE; CYCLOMETHICONE 5; ALCOHOL; PPG-14 BUTYL ETHER; ISOBUTANE; PROPANE; DISTEARDIMONIUM HECTORITE; ALKYL (C12-15) BENZOATE; SUNFLOWER OIL; DIMETHICONOL (40 CST); PROPYLENE CARBONATE; OCTYLDODECANOL; .ALPHA.-TOCOPHEROL ACETATE; BUTYLATED HYDROXYTOLUENE

Active Ingredient

Aluminum Chlorohydrate 20.2%

Purpose Antiperspirant

INDICATIONS AND USAGE

Use reduces underarm wetness

Warnings

Flammable. Do not use near heat, flame or while
smoking. Can cause serious Injury or death.
■ keep away from face and mouth to avoid
breathing in ■ avoid spraying in eyes. Contents
under pressure. Do not puncture or incinerate.
Do not expose to heal or store at temperature
above 120°F/SO"C or in enclosed places that
could overheat ■ do not use on broken skin.

Stop use if rash or irritation occurs

ask a doctor before using if you have kidney disease

Keep out of reach of children.

OTHER SAFETY INFORMATION

Use only as directed. Intentional misuse
by deliberately concentrating and Inhaling
the contents can be harmful or fatal.
Help stop inhalation abuse.
For information visit www.inhalant.org

DOSAGE AND ADMINISTRATION

Directions ■ hold can 6 inches away from
the underarm ■ apply to underarms only

Inactive Ingredients
butane, hydrofluorocarbon 152A, cyclopentasiloxane, alcohol denat.,
PPG-14 butyl ether, isobutane, propane, disteardimonium, hectorlte, C12-15 alkyl
benzoate, helianthus annuus (sunflower) seed oil, dimethiconol,
propylene carbonate, octyIdodecanol,
fragrance, tocopheryl acetate, BHT